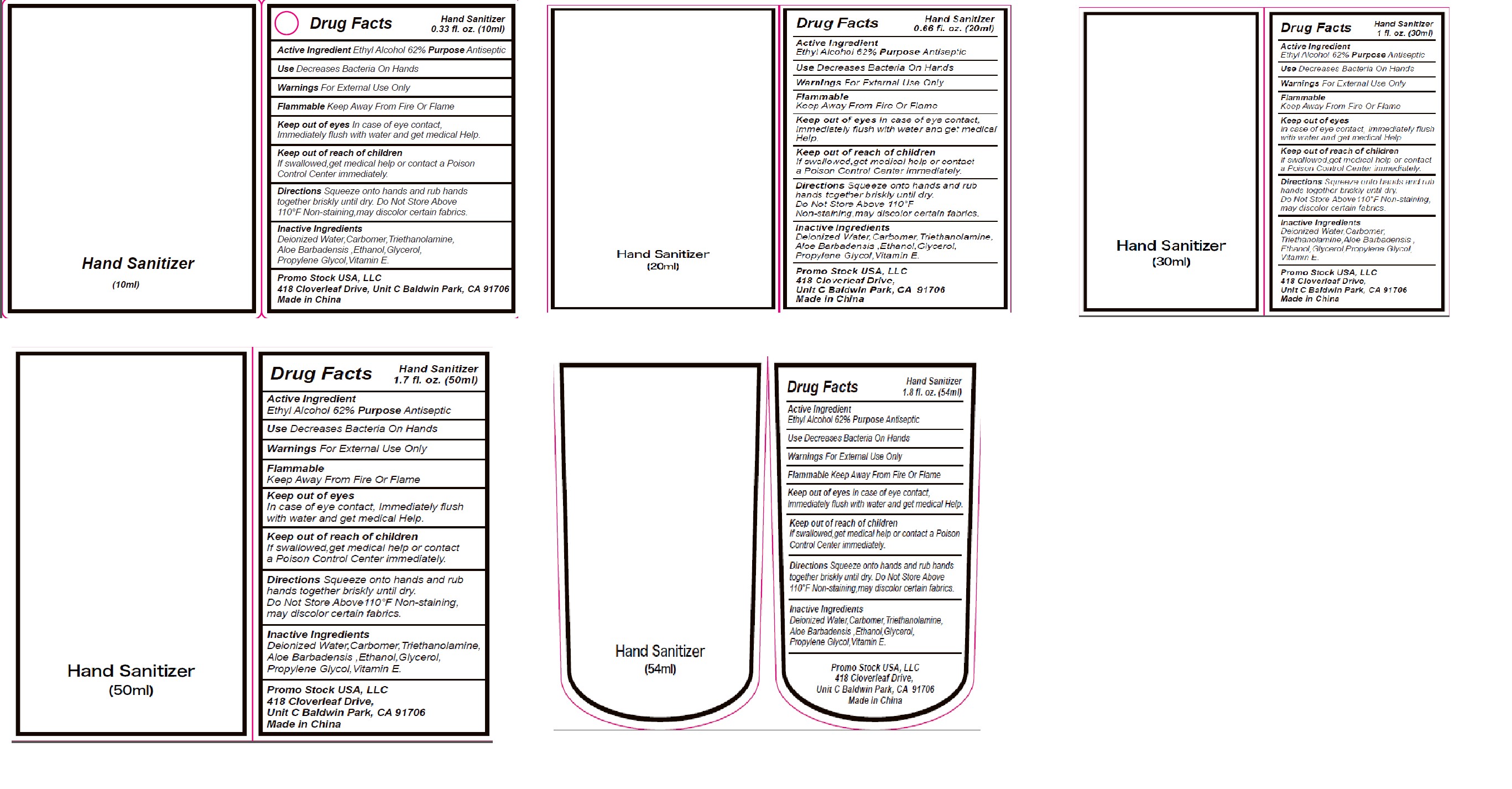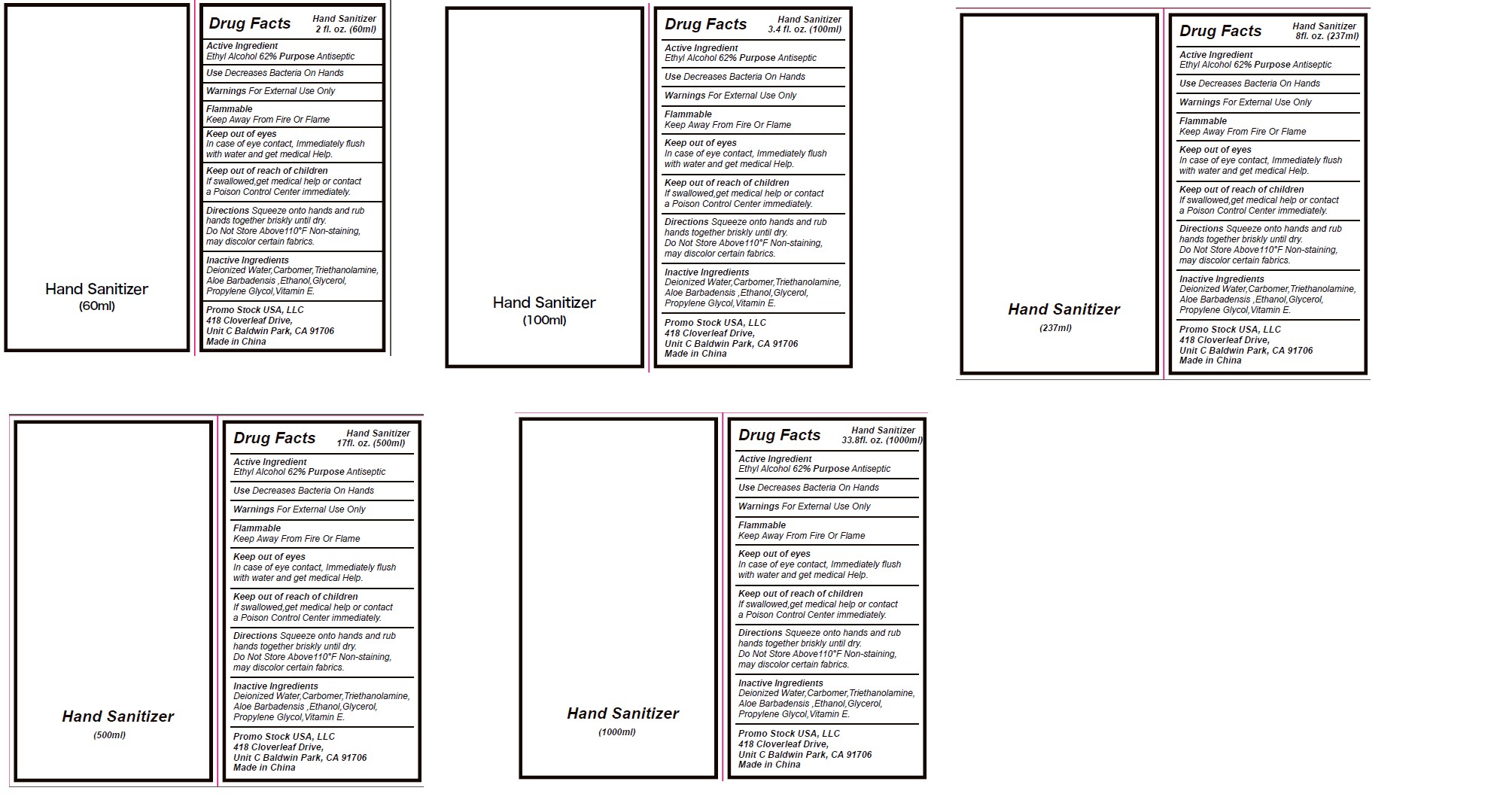 DRUG LABEL: Hand Sanitizer
NDC: 74034-006 | Form: GEL
Manufacturer: Sichuan Rejoy Essence Biotechnology Co., Ltd
Category: otc | Type: HUMAN OTC DRUG LABEL
Date: 20200506

ACTIVE INGREDIENTS: ALCOHOL 62 mL/100 mL
INACTIVE INGREDIENTS: PROPYLENE GLYCOL; TRICLOSAN; GLYCERIN; CARBOMER 934; WATER; TROLAMINE; ALOE VERA LEAF

Active Ingredient(s)

Ethyl Alcohol 62% Purpose Antiseptic

Purpose

Purpose Antiseptic

Uses

Decreases Bacteria On Hands

WARNINGS

For External Use Only

When using this product,do not use in or near the eyes.

When using this product keep out of eyes, ears, and mouth. In case of contact with eyes, rinse eyes thoroughly with water.
Stop use and ask a doctor if irritation or rash occurs. These may be signs of a serious condition.
Keep out of reach of children. If swallowed, get medical help or contact a Poison Control Center right away.

STOP USE

/

Keep out of reach of children

If swallowed,get medical help or contact a Poison
Control Center immediately.

Directions

Squeeze onto hands and rub hands
together briskly until dry. Do Not Store Above
110°F Non-staining,may discolor certain fabrics

Other information

Do Not Store Above
110°F Non-staining,may discolor certain fabrics

Inactive ingredients

Deionized Water,Carbomer,Triethanolamine,
Aloe Barbadensis ,Ethanol,Glycerol,
Propylene Glycol,Vitamin E.